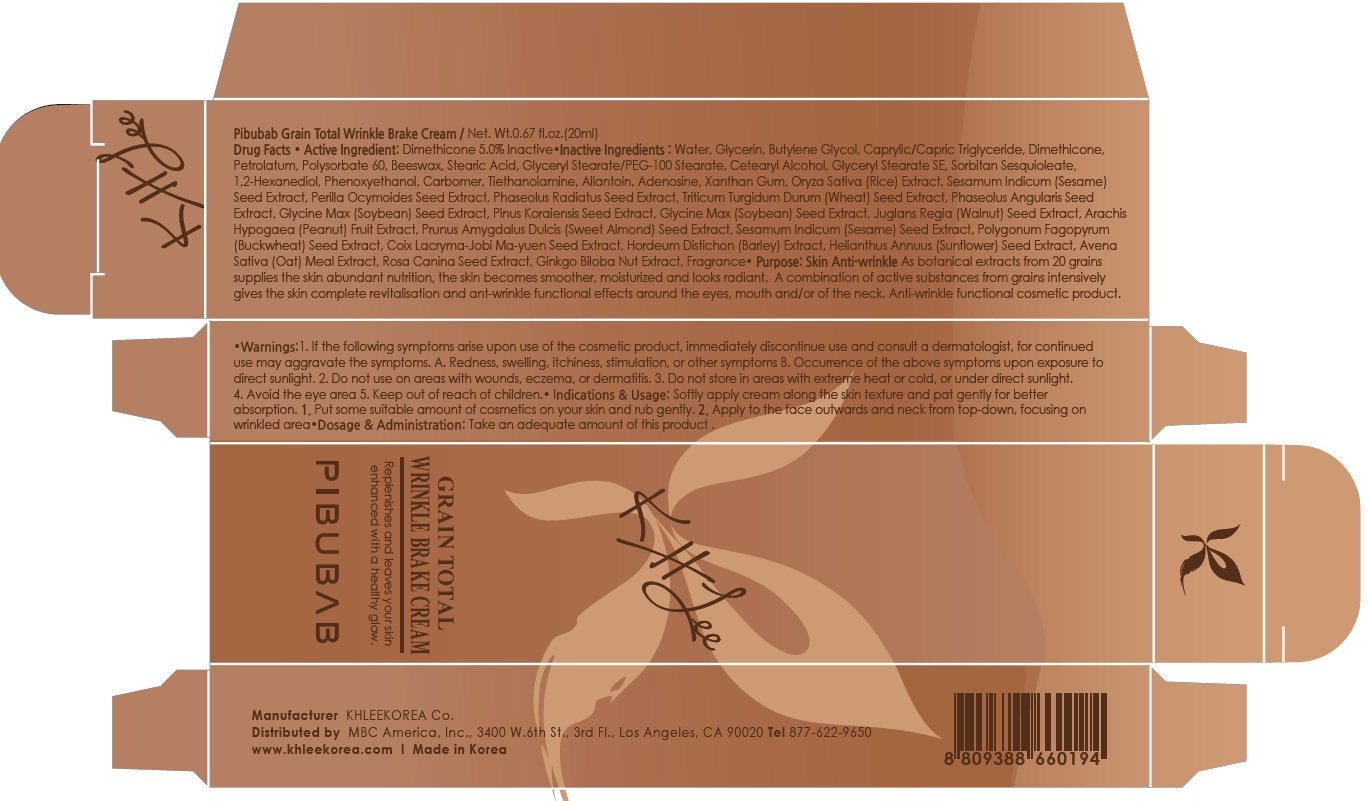 DRUG LABEL: Pibubab Grain Total Wrinkle Brake
NDC: 70567-030 | Form: CREAM
Manufacturer: KHLEEKOREA
Category: otc | Type: HUMAN OTC DRUG LABEL
Date: 20160418

ACTIVE INGREDIENTS: Dimethicone 1.0 g/20 mL
INACTIVE INGREDIENTS: Water; Glycerin

ACTIVE INGREDIENT

Active Ingredient: Dimethicone 5.0%

INACTIVE INGREDIENT

Inactive Ingredients: Water, Glycerin, Butylene Glycol, Caprylic/Capric Triglyceride, Petrolatum, Polysorbate 60, Beeswax, Stearic Acid, Glyceryl Stearate/PEG-100 Stearate, Cetearyl Alcohol, Glyceryl Stearate SE, Sorbitan Sesquioleate, 1,2-Hexanediol, Phenoxyethanol, Carbomer, Tiethanolamine, Allantoin, Adenosine, Xanthan Gum, Oryza Sativa (Rice) Extract, Sesamum Indicum (Sesame) Seed Extract, Perilla Ocymoides Seed Extract, Phaseolus Radiatus Seed Extract, Triticum Turgidum Durum (Wheat) Seed Extract, Phaseolus Angularis Seed Extract, Glycine Max (Soybean) Seed Extract, Pinus Koraiensis Seed Extract, Glycine Max (Soybean) Seed Extract, Juglans Regia (Walnut) Seed Extract, Arachis Hypogaea (Peanut) Fruit Extract, Prunus Amygdalus Dulcis (Sweet Almond) Seed Extract, Sesamum Indicum (Sesame) Seed Extract, Polygonum Fagopyrum (Buckwheat) Seed Extract, Coix Lacryma-Jobi Ma-yuen Seed Extract, Hordeum Distichon (Barley) Extract, Helianthus Annuus (Sunflower) Seed Extract, Avena Sativa (Oat) Meal Extract, Rosa Canina Seed Extract, Ginkgo Biloba Nut Extract, Fragrance

PURPOSE

Purpose: Skin Anti-wrinkle

As botanical extracts from 20 grains supplies the skin abundant nutrition, the skin becomes smoother, moisturized and looks radiant. A combination of active substances from grains intensively gives the skin complete revitalisation and ant-wrinkle functional effects around the eyes, mouth and/or of the neck. Anti-wrinkle functional cosmetic product.

WARNINGS

Warnings: 1. If the following symptoms arise upon use of the cosmetic product, immediately discontinue use and consult a dermatologist, for continued use may aggravate the symptoms. A. Redness, swelling, itchiness, stimulation, or other symptoms B. Occurrence of the above symptoms upon exposure to direct sunlight. 2. Do not use on areas with wounds, eczema, or dermatitis. 3. Do not store in areas with extreme heat or cold, or under direct sunlight. 4. Avoid the eye area 5. Keep out of reach of children

KEEP OUT OF REACH OF CHILDREN

INDICATIONS & USAGE

Indications & Usage: Softly apply cream along the skin texture and pat gently for better absorption. 1. Put some suitable amount of cosmetics on your skin and rub gently. 2. Apply to the face outwards and neck from tap-down, focusing on wrinkled area

DOSAGE & ADMINISTRATION

Dosage & Administration: Take an adequate amount of this product.